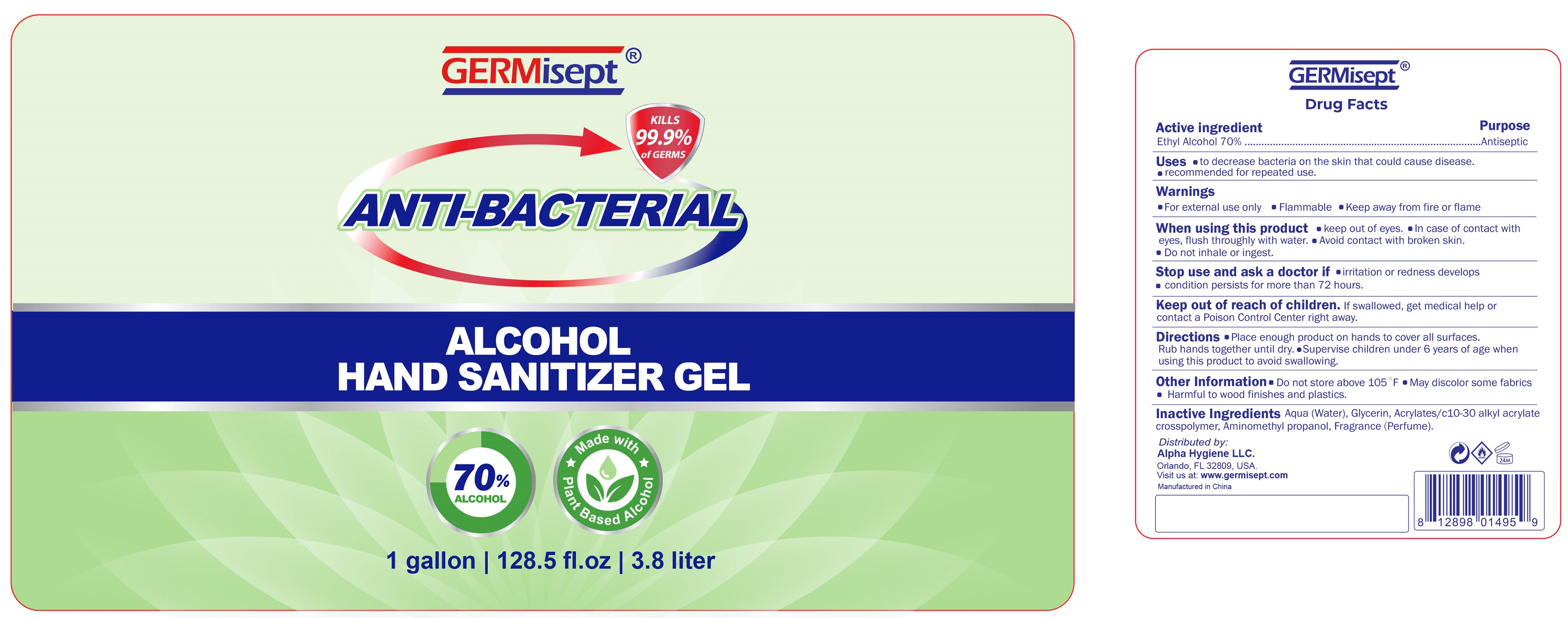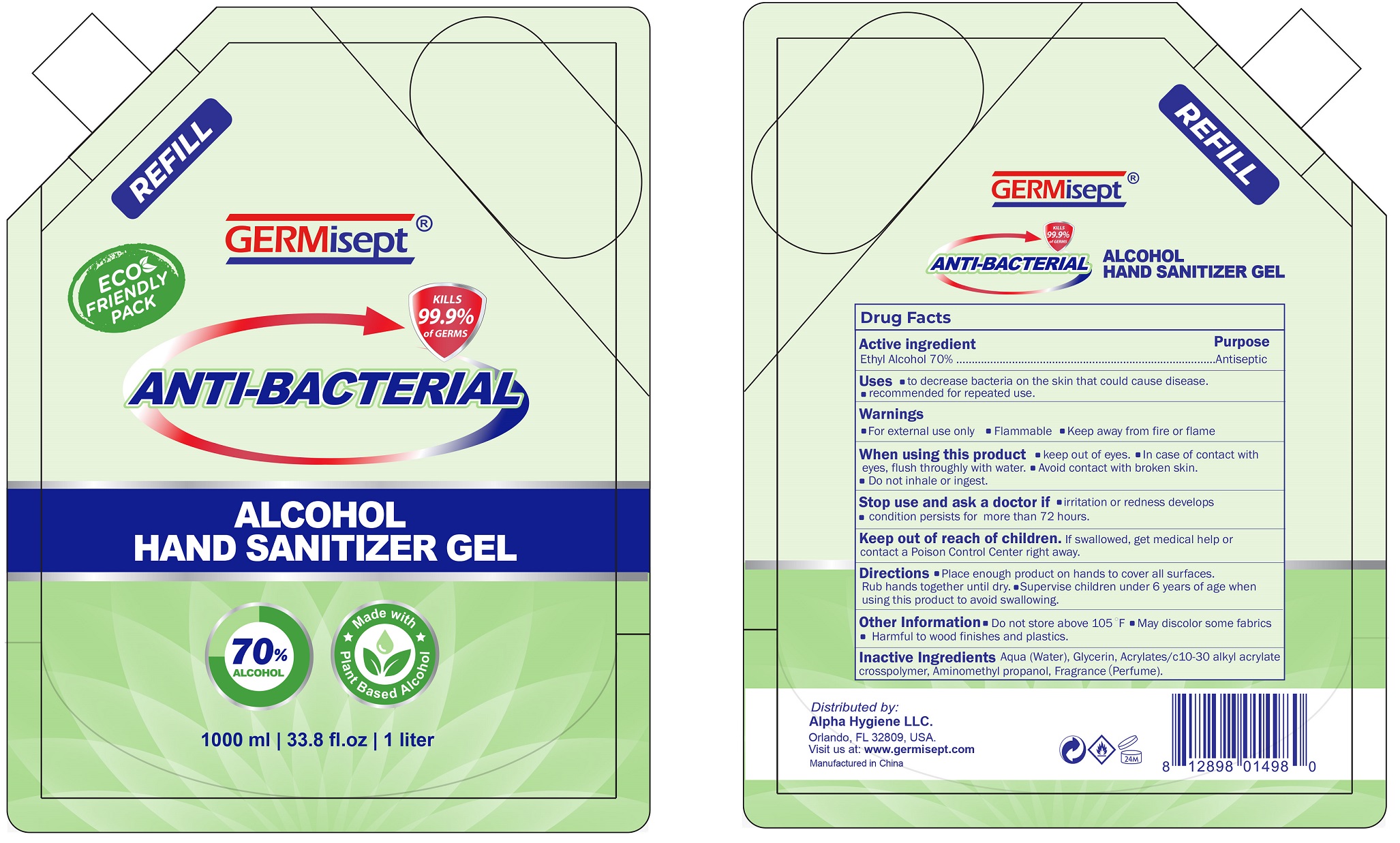 DRUG LABEL: Germisept Antibacterial Alcohol Hand Sanitizer
NDC: 80862-000 | Form: GEL
Manufacturer: Alpha Hygiene LLC
Category: otc | Type: HUMAN OTC DRUG LABEL
Date: 20201027

ACTIVE INGREDIENTS: ALCOHOL 0.7 mL/1 mL
INACTIVE INGREDIENTS: WATER; GLYCERIN; CARBOMER INTERPOLYMER TYPE A (ALLYL SUCROSE CROSSLINKED); AMINOMETHYLPROPANOL

Germisept Anti-Bacterial Alcohol Hand sanitizer Gel

Active ingredient

Ethyl Alcohol 70%

Purpose

Antiseptic

Uses

- to decrease bacteria on the skin that could cause disease.
- recommended for repeated use.

Warnings

- For external use only.
- Flammable.
- Keep away from heat or flame.

When using this product

- keep out of eyes.
- In case of contact with eyes, flush throughly with water.
- Avoid contact with broken skin.
- Do not inhale or ingest.

Stop use and ask a doctor if

- irritation or redness develops
- condition persists for more than 72 hours.

Keep out of reach of children.

If swallowed, get medical help or contact a Poison Control Center right away.

Directions

- Place enough product on hands to cover all surfaces. Rub hands together until dry.
- Supervise children under 6 years of age when using this product to avoid swallowing.

Other Information

- Do not store above 105°F
- May discolor some fabrics
- Harmful to wood finishes and plastics.

Inactive Ingredients

Aqua (Water), Glycerin, Acrylates/c10-30 alkyl acrylate crosspolymer, Aminomethyl propanol, Fragrance (Perfume).